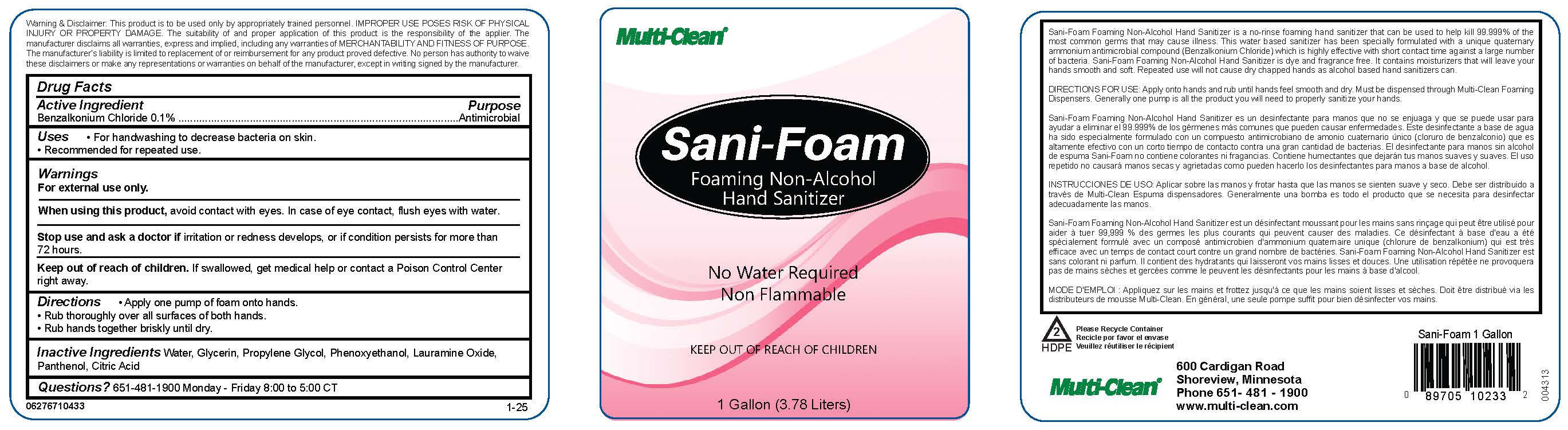 DRUG LABEL: Sani-Foam Foaming Non-Alcohol Hand Sanitizer
NDC: 62767-104 | Form: SOLUTION
Manufacturer: Multi-Clean
Category: otc | Type: HUMAN OTC DRUG LABEL
Date: 20251023

ACTIVE INGREDIENTS: BENZALKONIUM CHLORIDE 1 mg/1 mL
INACTIVE INGREDIENTS: LAURAMINE OXIDE; PANTHENOL; WATER; PHENOXYETHANOL; CITRIC ACID MONOHYDRATE; GLYCERIN; PROPYLENE GLYCOL

Sani-Foam Foaming Non-Alcohol Hand Sanitizer

Active Ingredient

Benzalkonium Chloride 0.1%

Purpose

Antimicrobial

Uses

- For handwashing to decrease bacteria on skin.
- Recommended for repeated use.

Warnings

For external use only.

When using this product, avoid contact with eyes. In case of eye contact, flush eyes with water.

Stop use and ask a doctor if irritation or redness develops, or if condition persists for more than 72 hours.

Keep out of reach of children. If swallowed, get medical help or contact a Poison Control Cener right away.

Directions

- Apply one pump of foam onto hands.
- Rub thoroughly over all surfaces of both hands.
- Rub hands together briskly until dry.

Inactive Ingredients

Water, Glycerin, Propylene Glycol, Phenoxyethanol, Lauramine Oxide, Panthenol, Citric Acid

Questions

651-481-1900 Monday - Friday 8:00 to 5:00 CT